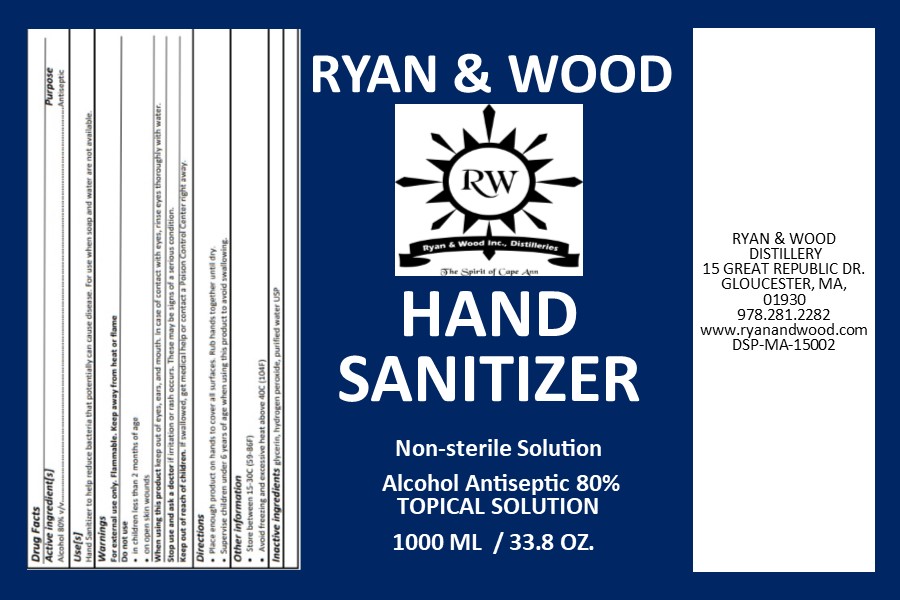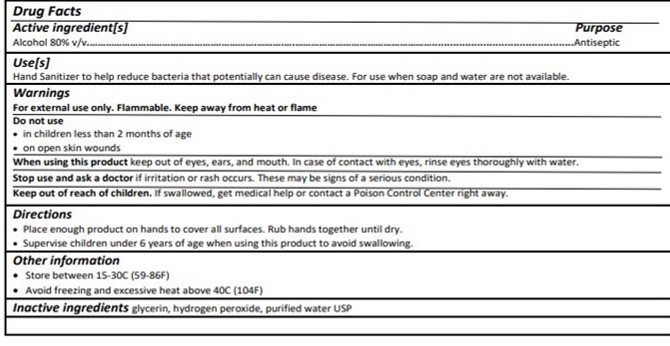 DRUG LABEL: Ryan and  Wood Ethanol Hand Sanitizer
NDC: 73886-0001 | Form: LIQUID
Manufacturer: Ryan & Wood Distillery
Category: otc | Type: HUMAN OTC DRUG LABEL
Date: 20201206

ACTIVE INGREDIENTS: ALCOHOL 800 mL/1000 mL
INACTIVE INGREDIENTS: WATER 143.8 mL/1000 mL; HYDROGEN PEROXIDE 41.7 mL/1000 mL; GLYCEROL FORMAL 14.5 mL/1000 mL

Ethanol Hand Sanitizer

Active Ingredient[s]

Alcohol 80% v/v....Antiseptic

Do Not Use

- in children less than 2 months of age
- in open skin wounds

Keep out of reach of children. If swallowed, get medical help or contact a Poison Control Center right away.

Purpose

Alcohol 80% v/v...Antiseptic

Stop use and ask a doctor if irritation or rash occurs. These may be signs of a serious condition.

When using this product keep out of eyes, ears and mouth. In case of contact with eyes, rinse eyes thoroughly with water.

Other Information

- Store between 15-30C (69-86F)
- Avoid freezing and excessive hear above 40C (104F)

Warnings

For external use only Flammable. Keep away from heat or flame

Do not use

in children less than 2 months of age

in open skinn wounds

When using this product keep out of eyes, ears and mouth. In case of contact with eyes, rinse eyes thoroughly with water.

Stop use and ask a doctor if irritation or rash occurs. These may be signs of a serious condition.

Keep out of reach of children. If swallowed, get medical help or contact a Poison Control Center right away.

Directions

- Place enough product on hands to cover all surfaces. Rub hands together until dry.
- Supervise children under 6 years of age when using this product to avoid swallowing.

Directions

Place enough product on hands to cover all surfaces. Rub hands together until dry.

Supervise children under 6 years of age when using this product to avoide swallowing.

Warnings

For external use only Flammable. Keep away from heat or flame

Do not use

in children less than 2 months of age
in open skinn wounds

When using this product keep out of eyes, ears and mouth. In case of contact with eyes, rinse eyes thoroughly with water.

Stop use and ask a doctor if irritation or rash occurs. These may be signs of a serious condition.

Keep out of reach of children. If swallowed, get medical help or contact a Poison Control Center right away.

Use[s]

Hand Sanitizer to help reduce bacterial that potentially can cause disease. For use when soap and water are not available.

Directions

Place enough product on hands to cover all surfaces. Rub hands together until dry.

Supervise children under 6 years of age when using this project to avoid swallowing.

Inactive Ingredients

Inactive Ingredients glycerin, hydrogen peroxide, purified water USP

Ryan & Wood Hand Sanitizer

RYAN & WOOD

HAND SANITIZER

Non-Sterile Solution

Alcohol Antiseptic 80%

TOPICAL SOLUTION

1000ML / 33.8OZ.

RYAN & WOOD DISTILLERY

15 GREAT REPUBLIC DRIVE

GLOUCESTER, MA 01930

978.281.2282

www.ryanandwood.com

DSP-MA-15002